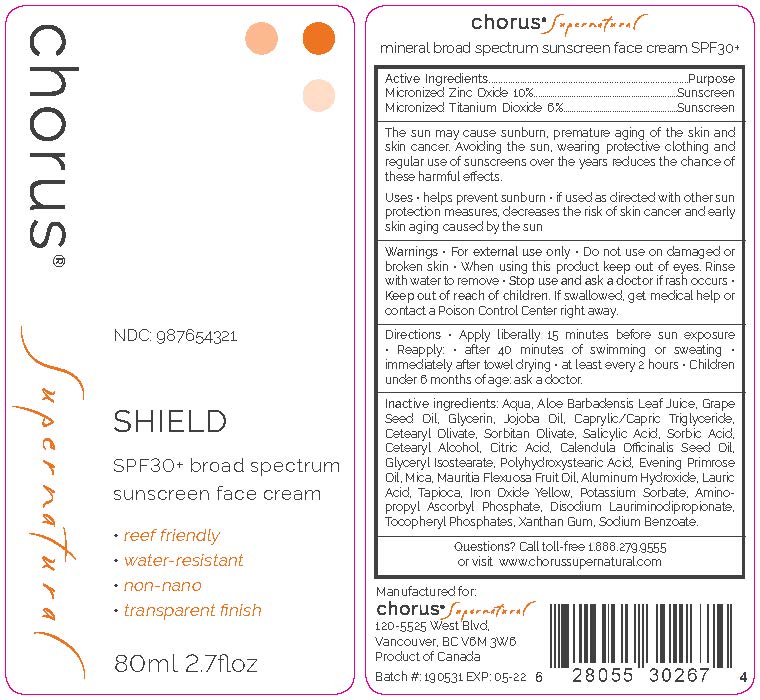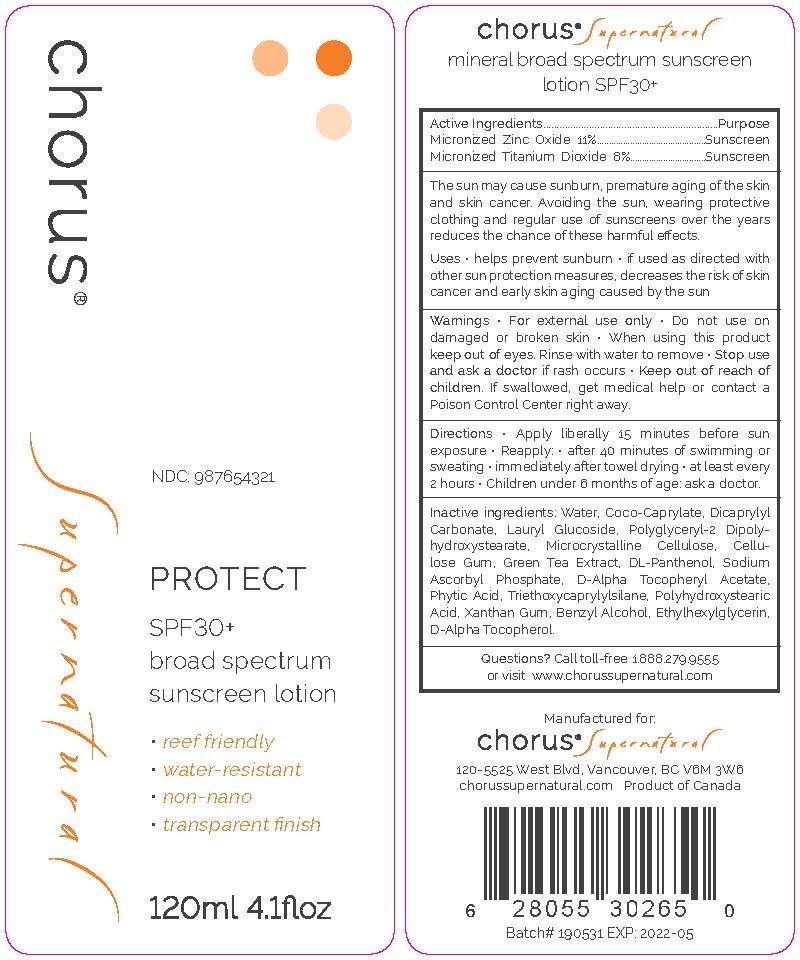 DRUG LABEL: chorus Supernatural PROTECT SPF 30 broad spectrum sunscreen
NDC: 69711-360 | Form: LOTION
Manufacturer: Derma Soleil
Category: otc | Type: HUMAN OTC DRUG LABEL
Date: 20190909

ACTIVE INGREDIENTS: ZINC OXIDE 11 g/100 mL; TITANIUM DIOXIDE 8 g/100 mL
INACTIVE INGREDIENTS: ETHYLHEXYLGLYCERIN; .ALPHA.-TOCOPHEROL, D-; COCO-CAPRYLATE/CAPRATE; DICAPRYLYL CARBONATE; GLYCERIN; CELLULOSE, MICROCRYSTALLINE; WATER; LAURYL GLUCOSIDE; GREEN TEA LEAF; PANTHENOL; SODIUM ASCORBYL PHOSPHATE; TOCOPHERYL NICOTINATE, D-.ALPHA.; FYTIC ACID; POLYHYDROXYSTEARIC ACID (2300 MW); TRIETHOXYCAPRYLYLSILANE; POLYGLYCERYL-2 DIPOLYHYDROXYSTEARATE; BENZYL ALCOHOL; CARBOXYMETHYLCELLULOSE CALCIUM; XANTHAN GUM

Chorus Supernatural

chorus Supernatural SHIELD SPF 30+ broad spectrum sunscreen face cream

PURPOSE

Micronized Zinc Oxide 10%..............Sunscreen

Micronized Titanium Dioxide 6%..............Sunscreen

ACTIVE INGREDIENT

Micronized Zinc 10%

Micronized Titanium Dioxide 6%

INDICATIONS AND USAGE

The sun may cause sunburn, premature aging of the skin and skin cancer. Avoiding the sun, wearing protective clothing and regular use of sunscreens over the years reduces the chance of these harmful effects.

Helps prevent sunburn

If used as directed with other sun protection measures, decreases the risk of skin cancer and early skin aging caused by sun

WARNINGS

For external use only.

Do not use on damaged or broken skin.

When using this product keep out of eyes. Rinse with water to remove.

Stop use and consult a doctor if rash occurs.

Keep out of reach of children.

If swallowed, get medical help or contact a Poison Control Center right away.

DOSAGE AND ADMINISTRATION

Apply liberally 15 minutes before sun exposure

Reapply

After 40 minutes of swimming or sweating

immediately after towel drying

at least every 2 hours

Children under 6 months of age: ask a doctor

INACTIVE INGREDIENT

Aqua, Aloe barbadensis Leaf Juice, Grape Seed Oil, Glycerine, Jojoba Oil,

Caprylic/Capric Triglyceride, Cetearyl Olivate, Sorbitan Olivate, Salicylic Acid, Sorbic Acid,

Cetearyl Alcohol, Citric Acid, Calendula officinalis Seed Oil, Glyceryl Isostearate,

Polyhydroxystearic Acid, Evening Primrose Oil, Mica, Mauritia flexuosa Fruit Oil, Aluminum Hydroxide,

Lauric Acid, Tapioca, Iron Oxide Yellow, Potassium Sorbate, Aminoprypyl Ascorbyl Phosphate,

Disodium Lauriminodipropionate Tocopheryl Phosphates, Xanthan Gum, Sodium Benzoate

chorus Supernatural PROTECT SPF30+ broad spectrum sunscreen lotion

PURPOSE

Sunscreen

ACTIVE INGREDIENT

Micronized Zinc Oxide 11%

Micronized Titanium Dioxide 8%

INDICATIONS AND USAGE

The sun may cause sunburn, premature aging of the skin and skin cancer. Avoiding the sun, wearing protective clothing and regular use of sunscreens over the years reduces the chance of these harmful effects.

Helps prevent sunburn

If used as directed with other sun protection measures, decreases the risk of skin cancer and early skin aging caused by sun

WARNINGS

For external use only.

Do not use on damaged or broken skin.

When using this product keep out of eyes. Rinse with water to remove.

Stop use and consult a doctor if rash occurs.

Keep out of reach of children.

If swallowed, get medical help or contact a Poison Control Center right away.

DOSAGE AND ADMINISTRATION

Apply liberally 15 minutes before sun exposure

Reapply

After 40 minutes of swimming or sweating

immediately after towel drying

at least every 2 hours

Children under 6 months of age: ask a doctor

INACTIVE INGREDIENT

Water, Coco-Caprylate, Dicaprylyl Carbonate, Lauryl Glucoside,

Polyglyceryl-2 Dipolyhydroxystearate, Glycerin, Microcrystalline Cellulose,

Cellulose Gum, Green Tea Extract, DL-Panthenol, Sodium Ascorbyl Phosphate,

D-alpha Tocopheryl Acetate, Phytic Acid, Triethoxycaprylylsilane, Polyhydroxystearic Acid,

Xanthan Gum, Benzyl Alcohol, Ethylhexylglycerin, D-alpha Tocopherol